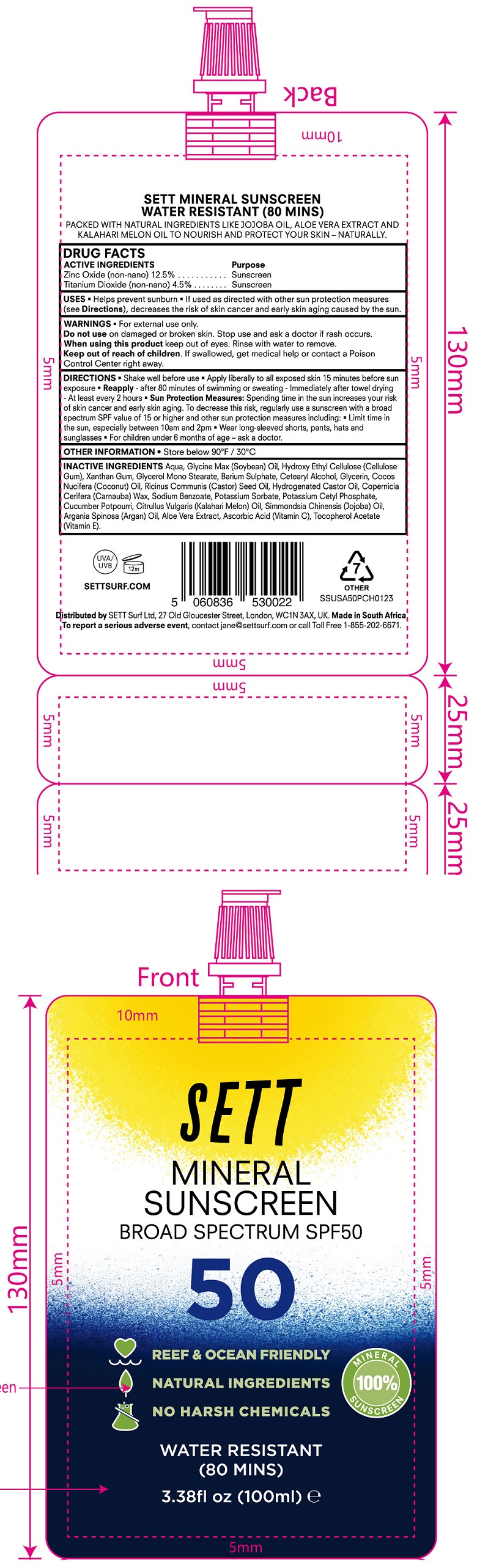 DRUG LABEL: SETT Mineral Sunscreen SPF 50
NDC: 83478-000 | Form: CREAM
Manufacturer: Sett Surf, Ltd.
Category: otc | Type: HUMAN OTC DRUG LABEL
Date: 20231106

ACTIVE INGREDIENTS: ZINC OXIDE 125 mg/1 mL; TITANIUM DIOXIDE 45 mg/1 mL
INACTIVE INGREDIENTS: WATER; SOYBEAN OIL; HYDROXYMETHYL CELLULOSE; XANTHAN GUM; BARIUM SULFATE; CETOSTEARYL ALCOHOL; GLYCERIN; COCONUT OIL; CASTOR OIL; HYDROGENATED CASTOR OIL; CARNAUBA WAX; SODIUM BENZOATE; POTASSIUM SORBATE; POTASSIUM CETYL PHOSPHATE; JOJOBA OIL; ARGAN OIL; ALOE VERA LEAF; ASCORBIC ACID; .ALPHA.-TOCOPHEROL ACETATE

SETT Mineral Sunscreen SPF 50

ACTIVE INGREDIENTS

Zinc Oxide (non-nano) 12.5%

Titanium Dioxide (non-nano) 4.5%

Purpose

Sunscreen

USES

- Helps prevent sunburn
- If used as directed with othe sun protection measures (see), decreases the risk of skin cancer and early skin aging caused by the sun. Directions

WARNINGS

For external use only.

Do not use

on damaged or broken skin.

Stop use and ask a doctor

if rash occurs.

When using this product

keep out of eyes. Rinse with water to remove.

Keep out of reach of children.

If swallowed, get medical help or contact a Poison Control Center right away.

DIRECTIONS

• Shake well before use • Apply liberally to all exposed skin 15 minutes before sun exposure • - after 80 minutes of swimming or sweating • Immediately after towel drying - At least every 2 hours • Sun Protection Measures: Spending time in the sun increaases your risk of skin cancer and early skin aging. To decrease this risk, regularly use a sunscreen with a broad spectrum SPF value of 15 or higher and other sun protection measres including: • Limit time in the sun, especially between 10am and 2pm • Wear long-sleeved shorts, pants, hats and sunglasses • For children under 6 months of age - ask a doctor. Reapply

OTHER INFORMATION

Store below 90ºF / 30ºC

INACTIVE INGREDIENTS

Aqua, Glycine Max (Soybean) Oil, Hydroxy Ethyl Cellulose (Cellulose Gum), Xanthan Gum, Glycerol Mono Stearate, Barium Sulphate, Cetearyl Alcohol, Glycerin, Cocos Nucifera (Coconut) Oil, Ricinus Communis (Castor) Seed Oil, Hydrogenated Castor Oil, Copernicia Cerifera (Carnauba) Wax, Sodium Benzoate, Potassium Sorbate, Potassium Cetyl Phosphate, Cucumber Potpourri, Citrullus Vulgaris (Kalahari Melon) Oil, Simmondsia Chenensis (Jojoba) Oil, Argania Spinosa (Argan) Oil, Aloe Vera Extract, Ascorbic Acid (Vitamin C), Tocopherol Acetate (Vitamin E).